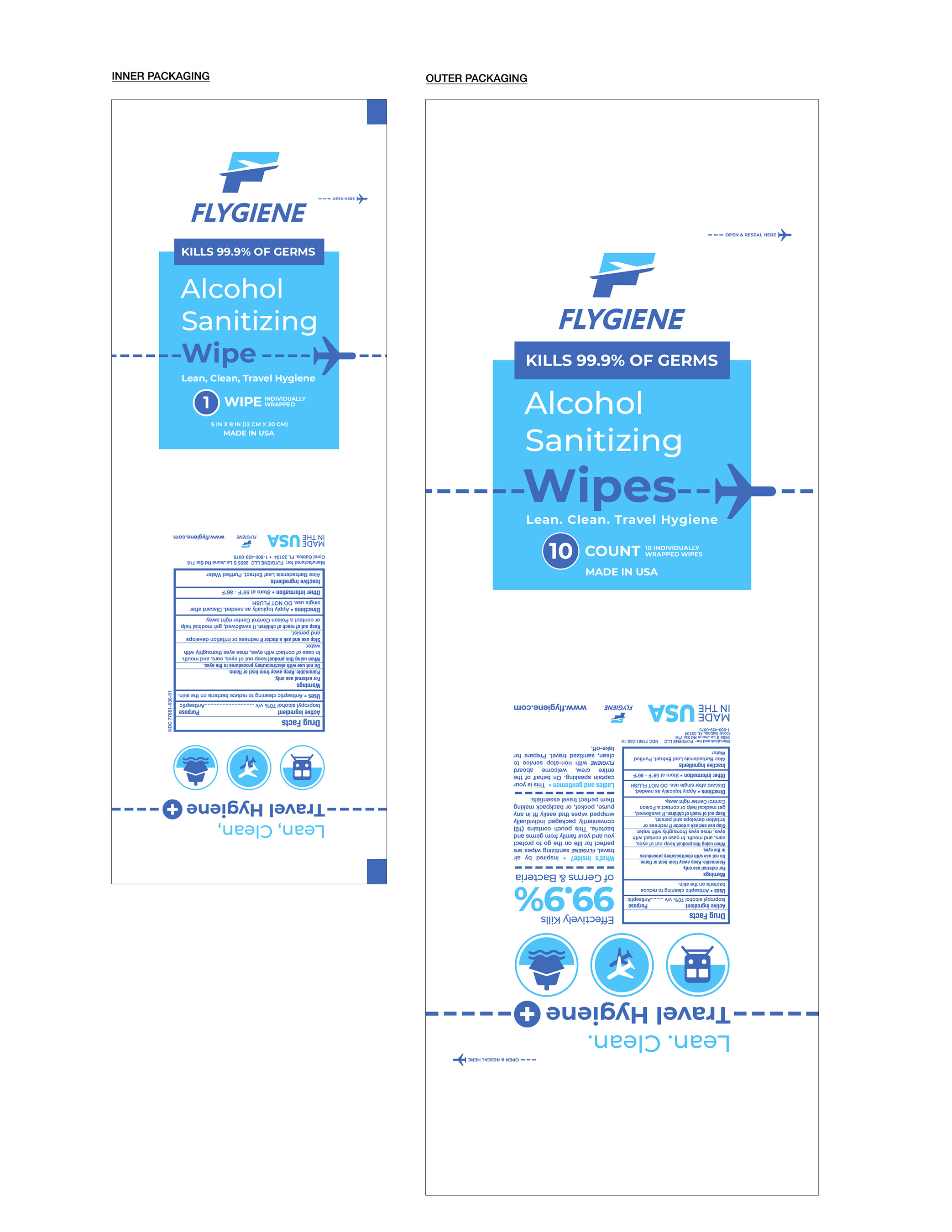 DRUG LABEL: FLYGIENE Alcohol Sanitizing Wipes
NDC: 77661-030 | Form: CLOTH
Manufacturer: FLYGIENE LLC
Category: otc | Type: HUMAN OTC DRUG LABEL
Date: 20230110

ACTIVE INGREDIENTS: ISOPROPYL ALCOHOL 70 mL/100 mL
INACTIVE INGREDIENTS: WATER; ALOE VERA LEAF

ACTIVE INGREDIENT

Isopropyl alcohol 70% v/v

PURPOSE

Antiseptic

INDICATIONS AND USAGE

Antiseptic cleaning to reduce bacteria on the skin.

WARNINGS

For external use only.
Flammable. Keep away from heat or flame.

Do not use with electrocautery procedures in the eyes.

When using this product keep out of eyes, ears, and mouth. In case of contact with eyes, rinse eyes thoroughly with water.

Stop use and ask a doctor if redness or irritation develops and persist.

Keep out of reach of children. If swallowed, get medical help or contact a Poison Control Center right away.

DOSAGE AND ADMINISTRATION

Apply topically as needed. Discard after single use. DO NOT FLUSH

[STORAGE AND HANDLING SECTION]

INACTIVE INGREDIENT

Aloe Barbadensis Leaf Extract, Purified Water